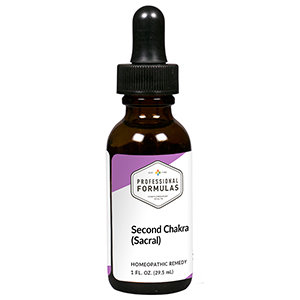 DRUG LABEL: Second Chakra (Sacral)
NDC: 63083-7302 | Form: LIQUID
Manufacturer: Professional Complementary Health Formulas
Category: homeopathic | Type: HUMAN OTC DRUG LABEL
Date: 20190815

ACTIVE INGREDIENTS: HELLEBORUS NIGER ROOT 8 [hp_X]/29.5 mL; STRYCHNOS IGNATII SEED 8 [hp_X]/29.5 mL; POTASSIUM CHLORATE 8 [hp_X]/29.5 mL; MAGNESIUM PHOSPHATE, DIBASIC TRIHYDRATE 8 [hp_X]/29.5 mL; ARTEMISIA CINA PRE-FLOWERING TOP 10 [hp_X]/29.5 mL; BOS TAURUS BILE 12 [hp_X]/29.5 mL; LACHESIS MUTA VENOM 12 [hp_X]/29.5 mL; SEPIA OFFICINALIS JUICE 12 [hp_X]/29.5 mL; SILICON DIOXIDE 30 [hp_X]/29.5 mL
INACTIVE INGREDIENTS: ALCOHOL; WATER

RCT2

ACTIVE INGREDIENTS

Helleborus niger 8X
Ignatia amara 8X
Kali chloricum 8X
Magnesia phosphorica 8X
Cina 10X
Fel tauri 12X
Lachesis mutus 12X
Sepia 12X
Carneol 30X, 60X, 100X
Rose quartz 30X, 60X, 100X

QUESTIONS

Professional Formulas

PO Box 2034 Lake Oswego, OR 97035

INDICATIONS

Temporarily relieves being overwhelmed, hypersensitivity, sadness, inability to trust, being cold and distant, or needy and dependent.*

PURPOSE

*Claims based on traditional homeopathic practice, not accepted medical evidence. Not FDA evaluated.

WARNINGS

In case of overdose, get medical help or contact a poison control center right away.

Keep out of the reach of children.

PREGNANCY OR BREAST FEEDING

If pregnant or breastfeeding, ask a healthcare professional before use.

DIRECTIONS

Place drops under tongue 30 minutes before/after meals. Adults and children 12 years and over: Take 5 drops up to 4 times per day for up to one month. Consult a physician for use in children under 12 years of age.

OTHER INFORMATION

Tamper resistant. If seal is broken, do not use. After opening, close container tightly and store at room temperature away from heat.

INACTIVE INGREDIENTS

20% ethanol, purified water.

LABEL

Est 1985

Professional Formulas

Complementary Health

Second Chakra (Sacral)

Homeopathic Remedy

1 FL. OZ. (29.5 mL)